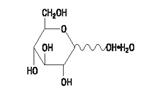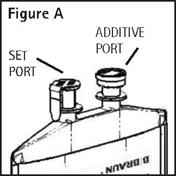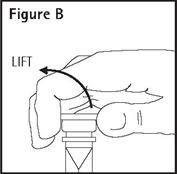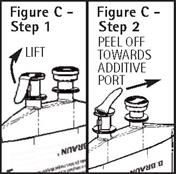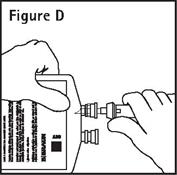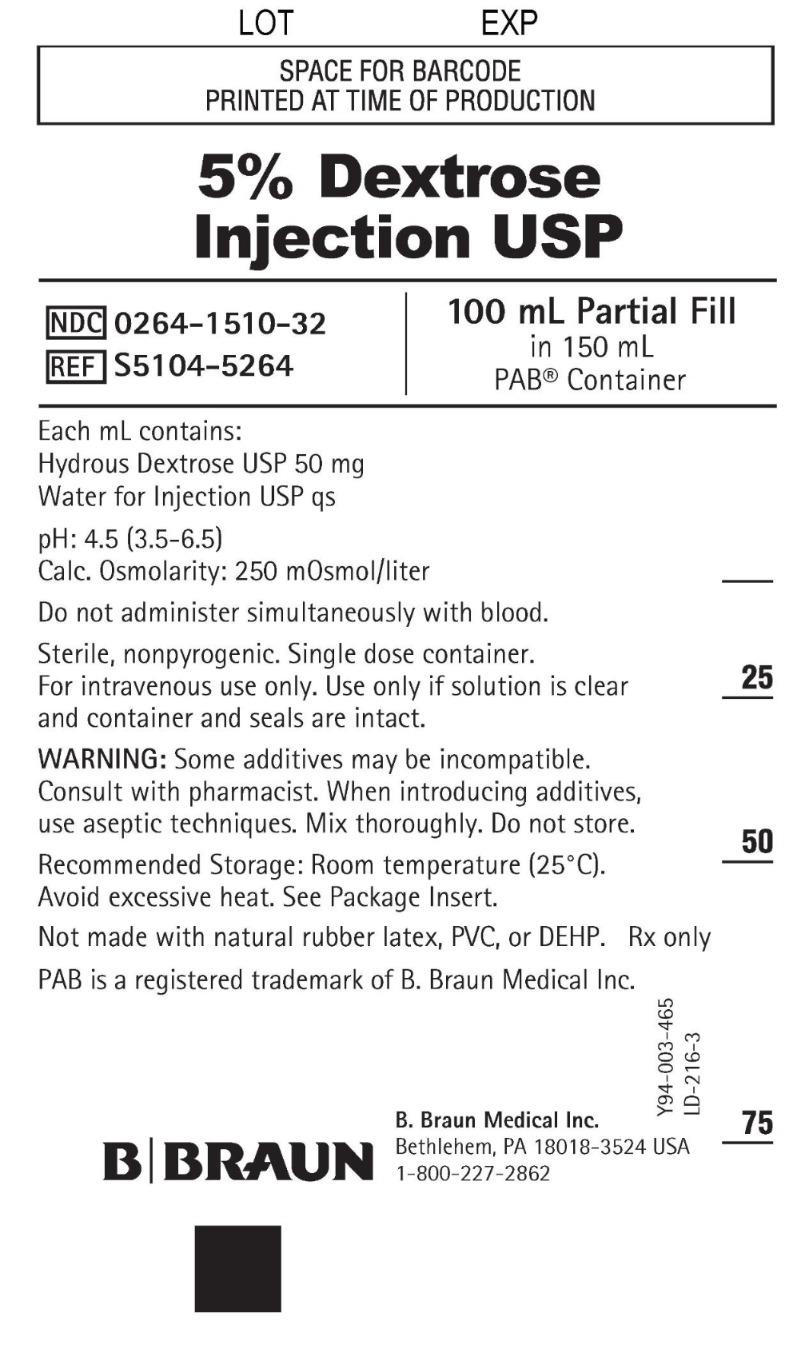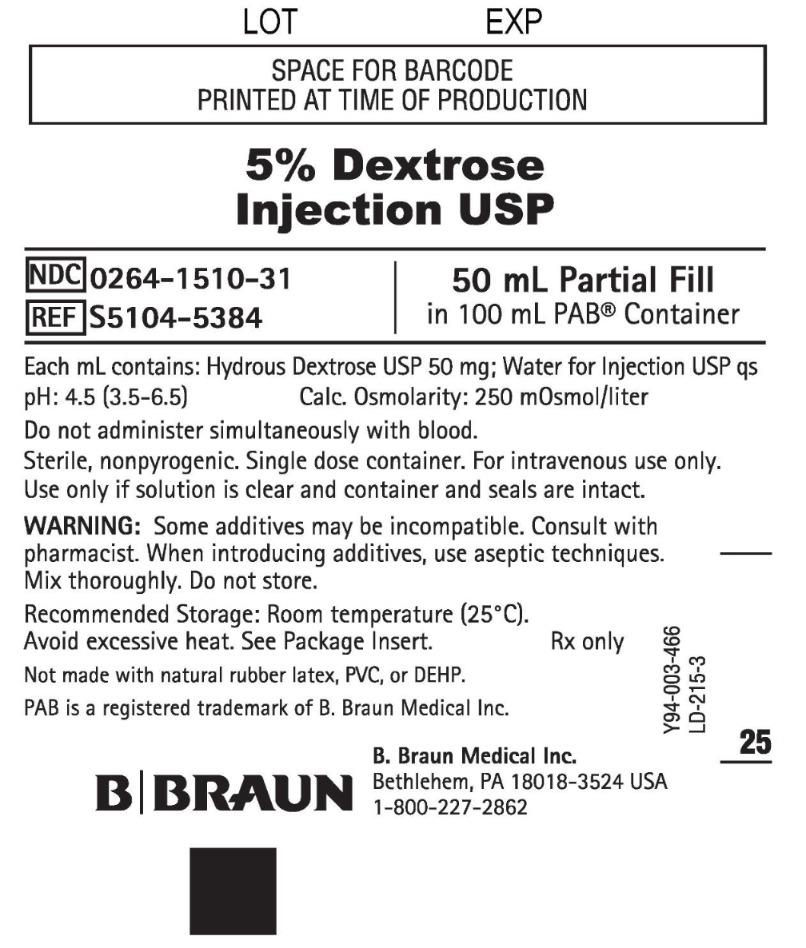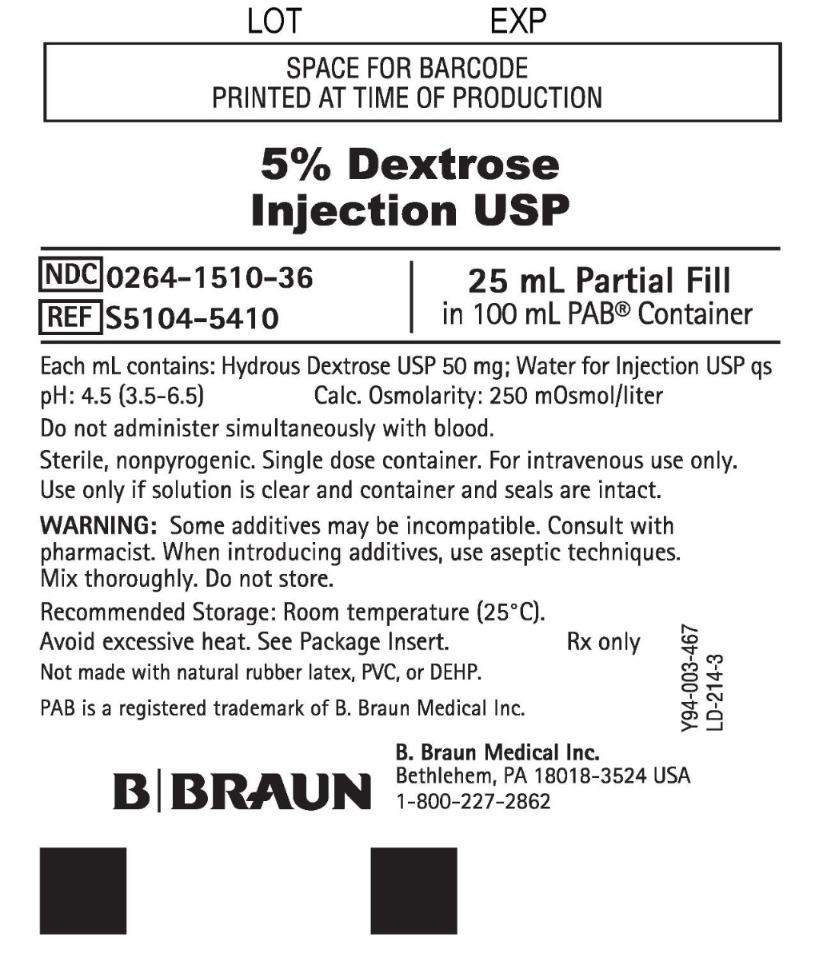 DRUG LABEL: Dextrose
NDC: 0264-1510 | Form: INJECTION, SOLUTION
Manufacturer: B. Braun Medical Inc.
Category: prescription | Type: HUMAN PRESCRIPTION DRUG LABEL
Date: 20240105

ACTIVE INGREDIENTS: DEXTROSE MONOHYDRATE 50 mg/1 mL
INACTIVE INGREDIENTS: WATER

5% Dextrose Injection USP

Partial Fill

DESCRIPTION

Each mL of 5% Dextrose Injection USP contains:
Hydrous Dextrose USP 50 mg; Water for Injection USP qs

pH: 4.5 (3.5–6.5)
Calculated Osmolarity: 250 mOsmol/liter
Calories per 100 mL: 17

This solution is sterile, nonpyrogenic, isotonic and contains no bacteriostatic or antimicrobial agents. This product is intended for intravenous administration.

The formula of the active ingredient is:

Ingredient | Molecular Formula | Molecular Weight
Hydrous Dextrose USP |  | 198.17

Not made with natural rubber latex, PVC, or DEHP.

The plastic container is a copolymer of ethylene and propylene formulated and developed for parenteral drugs. The copolymer contains no plasticizers and exhibits virtually no leachability. The safety of the plastic container has been confirmed by biological evaluation procedures. The material passes Class VI testing as specified in the U.S. Pharmacopeia for Biological Tests — Plastic Containers. These tests have shown that the container is nontoxic and biologically inert.

The container/solution unit is a closed system and is not dependent upon entry of external air during administration. The container has two ports, one is for the intravenous administration set and the other is a medication addition site. Each is covered by a tamperproof barrier. Refer to the Directions for Use of the container to properly identify the ports.

No vapor barrier is necessary.

CLINICAL PHARMACOLOGY

5% Dextrose Injection USP provides calories and is a source of water for hydration. It is capable of inducing diuresis depending on the volume administered and the clinical condition of the patient.

Dextrose is readily metabolized, may decrease losses of body protein and nitrogen, promotes glycogen deposition and decreases or prevents ketosis if sufficient doses are provided.

Water is an essential constituent of all body tissues and accounts for approximately 70% of total body weight. Average normal adult daily requirements range from two to three liters (1.0 to 1.5 liters each for insensible water loss by perspiration and urine production).

INDICATIONS AND USAGE

5% Dextrose Injection USP is indicated for use in adults and pediatric patients as sources of calories and water for hydration.

This product is designed for use as a diluent and delivery system for intermittent intravenous administration of compatible drug additives. Consult prescribing information for INDICATIONS AND USAGE of drug additives to be administered in this manner.

CONTRAINDICATIONS

Solutions containing dextrose may be contraindicated in patients with hypersensitivity to corn products.

Do not administer 5% Dextrose Injection USP simultaneously with blood through the same infusion set because hemolysis or pseudoagglutination may occur.

WARNINGS

The administration of intravenous solutions can cause fluid and/or solute overload resulting in dilution of serum electrolyte concentrations, overhydration, congested states or pulmonary edema. The risk of dilutional states is inversely proportional to the electrolyte concentrations of administered parenteral solutions.

Prolonged infusion of isotonic or hypotonic dextrose in water may increase the volume of extracellular fluid and cause water intoxication.

Solutions containing dextrose without electrolytes should not be administered simultaneously with blood through the same infusion set because of the possibility of agglomeration.

Excessive administration of potassium-free dextrose solutions may result in significant hypokalemia. Serum potassium levels should be maintained and potassium supplemented as required.

In very low birth weight infants, excessive or rapid administration of dextrose injection may result in increased serum osmolality and possible intracerebral hemorrhage.

PRECAUTIONS

General

This solution should be used with care in patients with hypervolemia, renal insufficiency, urinary tract obstruction, or impending or frank cardiac decompensation.

Solutions containing dextrose should be used with caution in patients with overt or known subclinical diabetes mellitus or carbohydrate intolerance for any reason.

To minimize the risk of possible incompatibilities arising from mixing this solution with other additives that may be prescribed, the final infusate should be inspected for cloudiness or precipitation immediately after mixing, prior to administration, and periodically during administration.

Laboratory Tests

Clinical evaluation and periodic laboratory determinations are necessary to monitor changes in fluid balance, electrolyte concentrations, and acid-base balance during prolonged parenteral therapy or whenever the condition of the patient warrants such evaluation. Significant deviations from normal concentrations may require tailoring of the electrolyte pattern, in this or an alternative solution(s).

Drug Interactions

Some additives may be incompatible. Consult with pharmacist. When introducing additives, use aseptic techniques. Mix thoroughly. Do not store.

Carcinogenesis, Mutagenesis, Impairment of Fertility

Studies with 5% Dextrose Injection USP have not been performed to evaluate carcinogenic potential, mutagenic potential or effects on fertility.

Pregnancy -

Teratogenic Effects

Animal reproduction studies have not been conducted with 5% Dextrose Injection USP. It is also not known whether 5% Dextrose Injection USP can cause fetal harm when administered to a pregnant woman or can affect reproduction capacity. 5% Dextrose Injection USP should be given to a pregnant woman only if clearly needed.

Labor and Delivery

As reported in the literature, dextrose solutions have been administered during labor and delivery. Caution should be exercised, and the fluid balance, glucose and electrolyte concentrations and acid-base balance, of both mother and fetus should be evaluated periodically or whenever warranted by the condition of the patient or fetus.

Nursing Mothers

Because many drugs are excreted in human milk, caution should be exercised when 5% Dextrose Injection USP is administered to a nursing woman.

Pediatric Use

The safety and effectiveness in the pediatric population are based on the similarity of the clinical conditions of the pediatric and adult populations.

In neonates or in very small infants even small volumes of fluid may affect fluid and electrolyte balance. Care must be exercised in treatment of neonates, especially pre-term neonates, whose renal function may be immature and whose ability to excrete fluid and solute loads may be limited. Fluid intake, urine output, and serum electrolytes should be monitored closely.

In very low birth weight infants, excessive or rapid administration of dextrose injection may result in increased serum osmolality and possible intracerebral hemorrhage.

Serum glucose concentrations should be frequently monitored when dextrose is prescribed to pediatric patients, particularly infants, neonates, and low birth weight infants. See WARNINGS and DOSAGE AND ADMINISTRATION.

Geriatric Use

An evaluation of current literature revealed no clinical experience identifying differences in responses between the elderly and younger patients. In general, dose selection for an elderly patient should be cautious, usually starting at the low end of the dosing range, reflecting the greater frequency of decreased hepatic, renal, or cardiac function, and of concomitant disease or other drug therapy.

This drug is known to be substantially excreted by the kidney, and the risk of toxic reactions to this drug may be greater in patients with impaired renal function. Because elderly patients are more likely to have decreased renal function, care should be taken in dose selection, and it may be useful to monitor renal function.

ADVERSE REACTIONS

Reactions which may occur because of the solution or the technique of administration include febrile response, infection at the site of injection, venous thrombosis or phlebitis extending from the site of injection, extravasation, and hypervolemia.

The physician should also be alert to the possibility of adverse reactions to drug additives diluted and administered from the plastic partial fill container. Prescribing information for drug additives to be administered in this manner should be consulted.

If an adverse reaction does occur, discontinue the infusion, evaluate the patient, institute appropriate therapeutic countermeasures, and save the remainder of the fluid for examination if deemed necessary.

OVERDOSAGE

In the event of a fluid or solute overload, reevaluate the patient's condition, and institute appropriate corrective treatment.

The administration of intravenous solutions can cause fluid and/or solute overload resulting in dilution of serum electrolyte concentrations, overhydration, congested states or pulmonary edema. The risk of dilutional states is inversely proportional to the electrolyte concentrations of administered parenteral solutions.

Prolonged infusion of isotonic or hypotonic dextrose in water may increase the volume of extracellular fluid and cause water intoxication.

DOSAGE AND ADMINISTRATION

This solution is for intravenous use only.

As directed by a physician. Dosage is dependent upon the age, weight, and clinical condition of the patient as well as laboratory determinations.

Do not use plastic container in series connection.

If administration is controlled by a pumping device, care must be taken to discontinue pumping action before the container runs dry or air embolism may result.

This solution is intended for intravenous administration using sterile equipment. It is recommended that intravenous administration apparatus be replaced at least once every 24 hours.

Use only if solution is clear and container and seals are intact.

When using this product as a diluent or vehicle for administration of drug additives, consult the prescribing information of the drug to be used.

Addition of medication should be accomplished using aseptic technique in order to assure sterility.

Physicochemical studies have shown that the container and solution can withstand freezing.

Some additives may be incompatible. Consult with pharmacist. When introducing additives, use aseptic techniques. Mix thoroughly. Do not store.

Parenteral drug products should be inspected visually for particulate matter and discoloration prior to administration, whenever solution and container permit.

Pediatric Use

As reported in the literature, the dosage and constant infusion rate of intravenous dextrose must be selected with caution in pediatric patients, particularly neonates and low birth weight infants, because of the increased risk of hyperglycemia/hypoglycemia.

There is no specific pediatric dose. The dose is dependent on weight, clinical condition, and laboratory results. Follow recommendations of appropriate pediatric reference text. See WARNINGS and PRECAUTIONS.

HOW SUPPLIED

5% Dextrose Injection USP is supplied sterile and nonpyrogenic in partial fill polyolefin containers. The 100/150 mL product is packaged 64 per case. The 50/100 mL product is packaged 84 per case. The 25/100 mL product is packaged 116 per case.

NDC | REF | Fill/Container (mL)
5% Dextrose Injection USP
0264-1510-36 | S5104-5410 | 25/100
0264-1510-31 | S5104-5384 | 50/100
0264-1510-32 | S5104-5264 | 100/150

STORAGE AND HANDLING

Exposure of pharmaceutical products to heat should be minimized. Avoid excessive heat. It is recommended that the product be stored at room temperature (25°C); however, brief exposure up to 40°C does not adversely affect the product.

Rx only

Revised: May 2022

PAB is a registered trademark of B. Braun Medical Inc.

Directions For Use of PAB® Container Partial Additive Bag

Aseptic technique is required.

Caution: Before use, perform the following checks: Read the label. Ensure solution is the one ordered and is within the expiration date.

Inspect the solution in good light for cloudiness, haze or particulate matter; check the container for leakage or damage. Any container which is suspect should not be used.

Use only if solution is clear and container and seals are intact. Single dose container. Discard unused portion. Consult Package Insert for complete product information.

The physician should also be alert to the possibility of adverse reactions to drug additives diluted and administered from the plastic partial fill container. Prescribing information for drug additives to be administered in this manner should be consulted.

Do not use plastic container in series connection.

This solution is intended for intravenous administration using sterile equipment. It is recommended that intravenous administration apparatus be replaced at least once every 24 hours.

Physicochemical studies have shown that the container and solution can withstand freezing.

1. Identify Two Ports (See Figure A).
2. To Add Medication
  Remove additive port closure: hold container below additive port and grasp cap between thumb and forefinger then flip cap upward (See Figure B). Swab exposed additive port. Using a syringe with 18 gauge or smaller needle, insert cannula through resealable additive port and add desired drug. Mix thoroughly.
  Note: Partial fill bags have been designed to accept an overfill of up to 50 mL.
3. To Attach Administration Set
  To aseptically remove the set port closure: hold container below the set port and grasp the foil tab between the thumb and forefinger then pull the tab in two steps as shown in Figure C Steps 1 and 2.
4. Push spike through the diaphragm of the port (See Figure D). Hang container using hole on the lower flap. Prime set in accordance with the Directions for Use provided with the set in use.

When the container is to be used as a diluent and delivery system for intermittent intravenous administration of compatible drug additives, consult prescribing information for INDICATIONS AND USAGE of drug additives to be administered in this manner.

Warning: Some additives may be incompatible. Consult with pharmacist. When introducing additives, use aseptic techniques. Mix thoroughly. Do not store.

PAB containers can be safely transported in a standard 6-inch carrier through a pneumatic tube system that is well maintained and running properly.

B. Braun Medical Inc.
Bethlehem, PA 18018-3524 USA
1-800-227-2862

Y36-003-061 LD-213-6

PRINCIPAL DISPLAY PANEL - 100 mL Partial Fill

5% Dextrose
Injection USP

NDC 0264-1510-32
REF S5104-5264

100 mL Partial Fill
in 150 mL
PAB® Container

Each mL contains:
Hydrous Dextrose USP 50 mg
Water for Injection USP qs
pH: 4.5 (3.5-6.5)
Calc. Osmolarity: 250 mOsmol/liter
Do not administer simultaneously with blood.
Sterile, nonpyrogenic. Single dose container.
For intravenous use only. Use only if solution is clear
and container and seals are intact.
WARNING: Some additives may be incompatible.
Consult with pharmacist. When introducing additives,
use aseptic techniques. Mix thoroughly. Do not store.
Recommended Storage: Room temperature (25°C).
Avoid excessive heat. See Package Insert.
Not made with natural rubber latex, PVC, or DEHP. Rx only
PAB is a registered trademark of B. Braun Medical Inc.

B. Braun Medical Inc.
Bethlehem, PA 18018-3524 USA
1-800-227-2862

Y94-003-465 LD-216-3

LOT EXP

PRINCIPAL DISPLAY PANEL - 50 mL Partial Fill

5% Dextrose
Injection USP

NDC 0264-1510-31
REF S5104-5384

50 mL Partial Fill
in 100 mL PAB® Container

Each mL contains: Hydrous Dextrose USP 50 mg; Water for Injection USP qs
pH: 4.5 (3.5-6.5) Calc. Osmolarity: 250 mOsmol/liter
Do not administer simultaneously with blood.
Sterile, nonpyrogenic. Single dose container. For intravenous use only.
Use only if solution is clear and container and seals are intact.

WARNING: Some additives may be incompatible. Consult with
pharmacist. When introducing additives, use aseptic techniques.
Mix thoroughly. Do not store.

Recommended Storage: Room temperature (25°C).
Avoid excessive heat. See Package Insert. Rx Only
Not made with natural rubber latex, PVC, or DEHP.

PAB is a registered trademark of B. Braun Medical Inc.

B. Braun Medical Inc.
Bethlehem, PA 18018-3524 USA
1-800-227-2862

Y94-003-466 LD-215-3

LOT EXP

PRINCIPAL DISPLAY PANEL - 25 mL Partial Fill

5% Dextrose
Injection USP

NDC 0264-1510-36
REF S5104-5410

25 mL Partial Fill
in 100 mL PAB® Container

Each mL contains: Hydrous Dextrose USP 50 mg; Water for Injection USP qs
pH: 4.5 (3.5-6.5) Calc. Osmolarity: 250 mOsmol/liter

Do not administer simultaneously with blood.
Sterile, nonpyrogenic. Single dose container. For intravenous use only.
Use only if solution is clear and container and seals are intact.

WARNING: Some additives may be incompatible. Consult with
pharmacist. When introducing additives, use aseptic techniques.
Mix thoroughly. Do not store.

Recommended Storage: Room temperature (25°C).
Avoid excessive heat. See Package Insert. Rx only
Not made with natural rubber latex, PVC, or DEHP.

PAB is a registered trademark of B. Braun Medical Inc.

B. Braun Medical Inc.
Bethlehem, PA 18018-3524 USA
1-800-227-2862

Y94-003-467 LD-214-3

LOT EXP